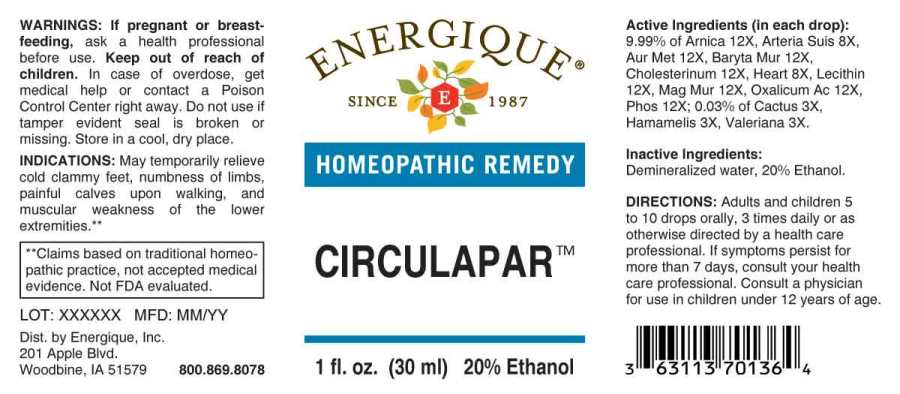 DRUG LABEL: Circulapar
NDC: 44911-0465 | Form: LIQUID
Manufacturer: Energique, Inc.
Category: homeopathic | Type: HUMAN OTC DRUG LABEL
Date: 20241024

ACTIVE INGREDIENTS: SELENICEREUS GRANDIFLORUS STEM 3 [hp_X]/1 mL; HAMAMELIS VIRGINIANA ROOT BARK/STEM BARK 3 [hp_X]/1 mL; VALERIAN 3 [hp_X]/1 mL; SUS SCROFA ARTERY 8 [hp_X]/1 mL; PORK HEART 8 [hp_X]/1 mL; ARNICA MONTANA WHOLE 12 [hp_X]/1 mL; GOLD 12 [hp_X]/1 mL; BARIUM CHLORIDE DIHYDRATE 12 [hp_X]/1 mL; CHOLESTEROL 12 [hp_X]/1 mL; SOYBEAN LECITHIN 12 [hp_X]/1 mL; MAGNESIUM CHLORIDE 12 [hp_X]/1 mL; OXALIC ACID 12 [hp_X]/1 mL; PHOSPHORUS 12 [hp_X]/1 mL
INACTIVE INGREDIENTS: WATER; ALCOHOL

DRUG FACTS:

ACTIVE INGREDIENTS:

(in each drop): 9.99% of Arnica Montana 12X, Arteria Suis 8X, Aurum Metallicum 12X, Baryta Muriatica 12X, Cholesterinum 12X, Heart (Suis) 8X, Lecithin 12X, Magnesia Muriatica 12X, Oxalicum Acidum 12X, Phosphorus 12X; 0.03% of Cactus Grandiflorus 3X, Hamamelis Virginiana 3X, Valeriana Officinalis 3X.

INDICATIONS:

May temporarily relieve cold clammy feet, numbness of limbs, painful calves upon walking, and muscular weakness of the lower extremities.**

**Claims based on traditional homeopathic practice, not accepted medical evidence. Not FDA evaluated.

WARNINGS:

If pregnant or breastfeeding, ask a health professional before use.

Keep out of reach of children. In case of overdose, get medical help or contact a Poison Control Center right away.

Do not use if tamper evident seal is broken or missing.

Store in a cool, dry place.

Keep out of reach of children. In case of overdose, get medical help or contact a Poison Control Center right away.

DIRECTIONS:

Adults and children 5 to 10 drops orally, 3 times daily or as otherwise directed by a health care professional. If symptoms persist for more than 7 days, consult your health care professional. Consult a physician for use in children under 12 years of age.

INDICATIONS:

May temporarily relieve cold clammy feet, numbness of limbs, painful calves upon walking, and muscular weakness of the lower extremities.**

**Claims based on traditional homeopathic practice, not accepted medical evidence. Not FDA evaluated.

INACTIVE INGREDIENTS:

Demineralized water, 20% Ethanol.

QUESTIONS:

Dist. by Energique, Inc.
201 Apple Blvd.
Woodbine, IA 51579 800.869.8078

PACKAGE LABEL DISPLAY:

ENERGIQUE

SINCE 1987

HOMEOPATHIC REMEDY

CIRCULAPAR

1 fl. oz. (30 ml)